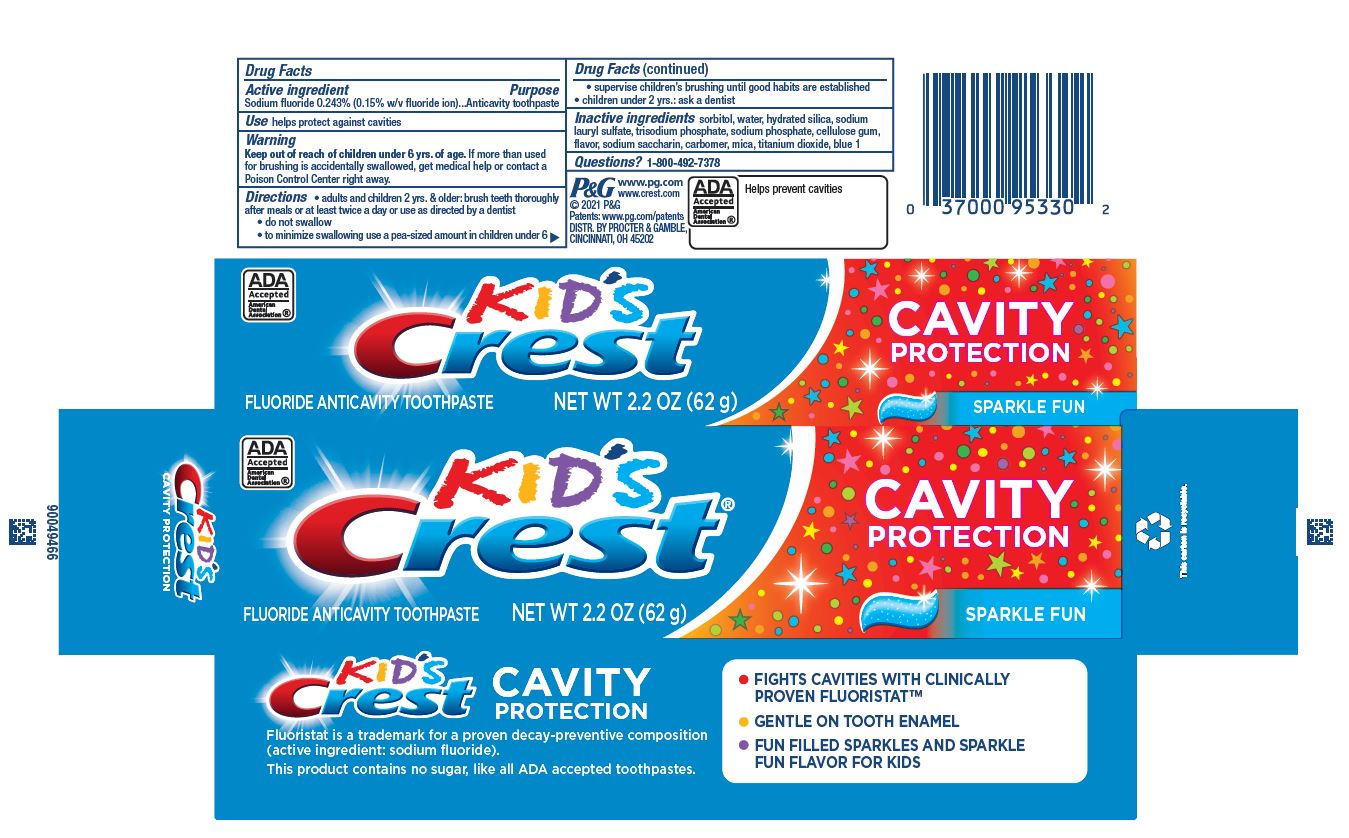 DRUG LABEL: Kids Crest Cavity Protection
NDC: 37000-049 | Form: PASTE, DENTIFRICE
Manufacturer: The Procter & Gamble Manufacturing Company
Category: otc | Type: HUMAN OTC DRUG LABEL
Date: 20260212

ACTIVE INGREDIENTS: SODIUM FLUORIDE 1.5 mg/1 g
INACTIVE INGREDIENTS: CARBOXYMETHYLCELLULOSE SODIUM; SORBITOL; SACCHARIN SODIUM; WATER; HYDRATED SILICA; SODIUM LAURYL SULFATE; SODIUM PHOSPHATE; MICA; TITANIUM DIOXIDE; FD&C BLUE NO. 1; SODIUM PHOSPHATE, TRIBASIC, ANHYDROUS; CARBOMER

Kid's Crest Cavity Protection

Drug Facts

Active ingredient

Sodium fluoride 0.243% (0.15% w/v fluoride ion)

Purpose

Anticavity toothpaste

Use

helps protect against cavities

Warnings

Keep out of reach of children under 6 yrs. of age.

WHEN USING

If more than used for brushing is accidentally swallowed, get medical help or contact a Poison Control Center right away.

Directions

- adults and children 2 yrs. & older: brush teeth thoroughly after meals or at least twice a day or use as directed by a dentist
  - do not swallow
  - to minimize swallowing use a pea-sized amount in children under 6
  - supervise children's brushing until good habits are established
- children under 2 yrs.: ask a dentist

Inactive ingredients

sorbitol, water, hydrated silica, sodium lauryl sulfate, trisodium phosphate, sodium phosphate, cellulose gum, flavor, sodium saccharin, carbomer, mica, titanium dioxide, blue 1

Questions?

1-800-492-7378

PRINCIPAL DISPLAY PANEL - 62 g carton

Kid's Crest

FLUORIDE ANTICAVITY TOOTHPASTE

NET WT 2.2 OZ (62 g)

CAVITY PROTECTION

SPARKLE FUN